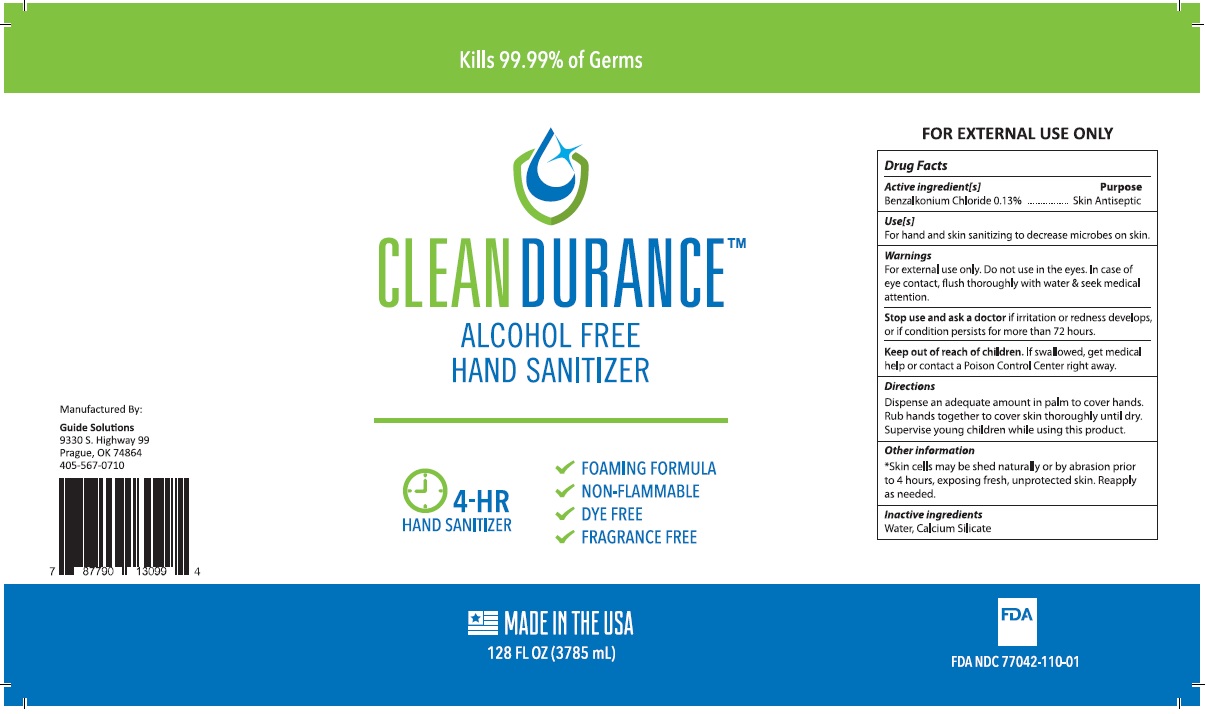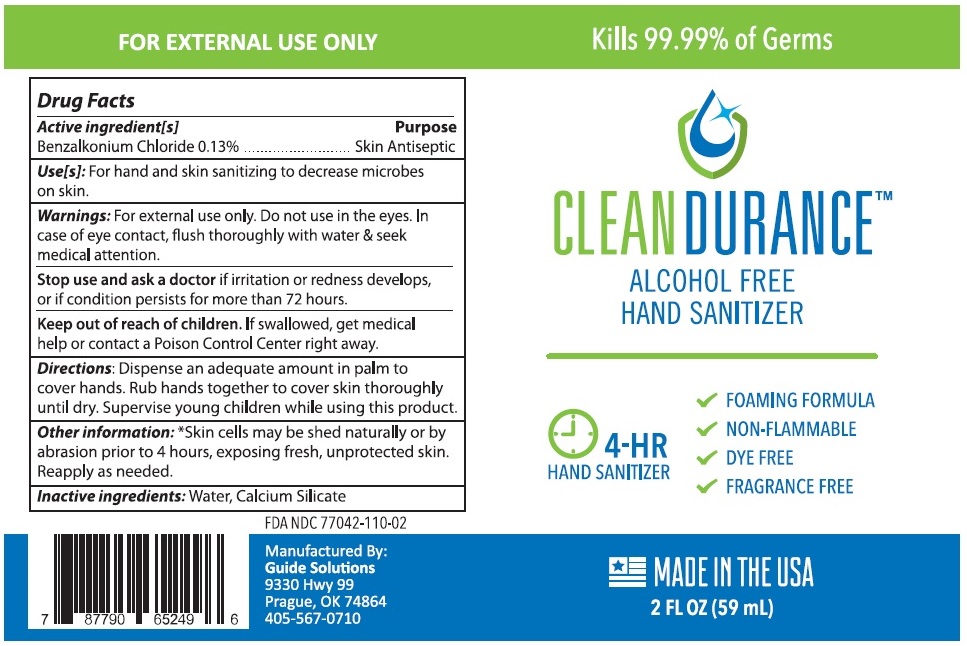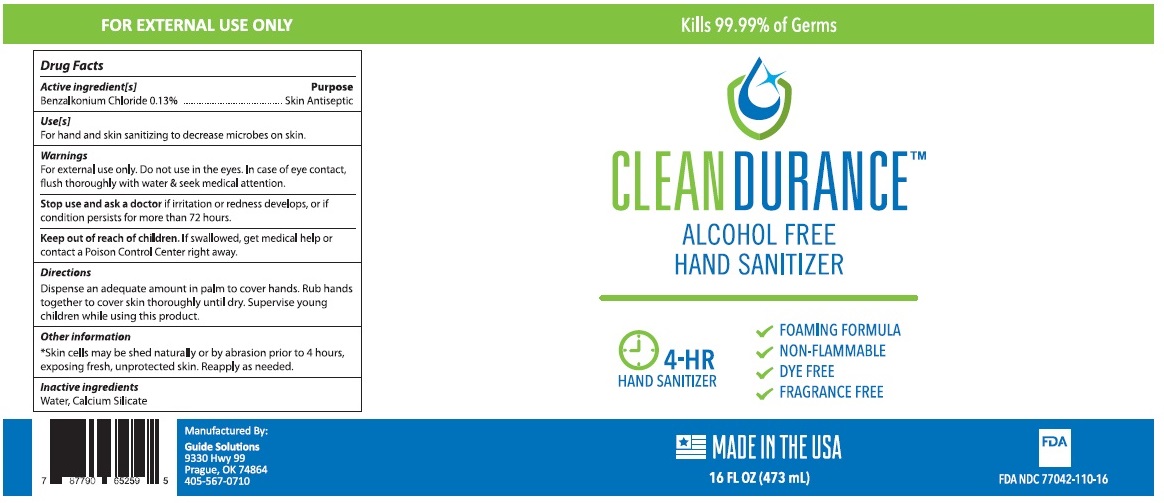 DRUG LABEL: Alcohol Free Hand Sanitizer
NDC: 77042-110 | Form: LIQUID
Manufacturer: Guide Energy Solutions LLC
Category: otc | Type: HUMAN OTC DRUG LABEL
Date: 20201028

ACTIVE INGREDIENTS: BENZALKONIUM CHLORIDE 0.13 g/100 mL
INACTIVE INGREDIENTS: WATER; CALCIUM SILICATE

CLEANDURANCETM ALCOHOL FREE HAND SANITIZER

Active ingredient[s]

Benzalkonium Chloride 0.13%

Purpose

Skin Antiseptic

Use[s]

For hand and skin sanitizing to decrease microbes on skin.

Warnings

For external use only. Do not use in the eyes. In case of eye contact, flush thoroughly with water & seek medical attention.

Stop use and ask a doctor if irritation or redness develops, or if condition persists for more than 72 hours.

Keep out of reach of children. If swallowed, get medical help or contact a Poison Control Center right away.

Directions

Dispense an adequate amount in palm to cover hands.

Rub hands together to cover skin thoroughly until dry.

Supervise young children while using this product.

Other information

*Skin cells may be shed naturally or by abrasion prior to 4 hours, exposing fresh, unprotected skin. Reapply as needed.

Inactive ingredients

Water, Calcium Silicate

Kills 99.99% of Bacteria & Viruses

4-HR HAND SANITIZER

• NON-FLAMMABLE

• NON-TOXIC

• DYE FREE

• FRAGRANCE FREE

MADE IN THE USA

Manufactured By:

Guide Solutions
9330 S. Highway 99
Prague, OK 74864
405-567-0710

FDA Registered